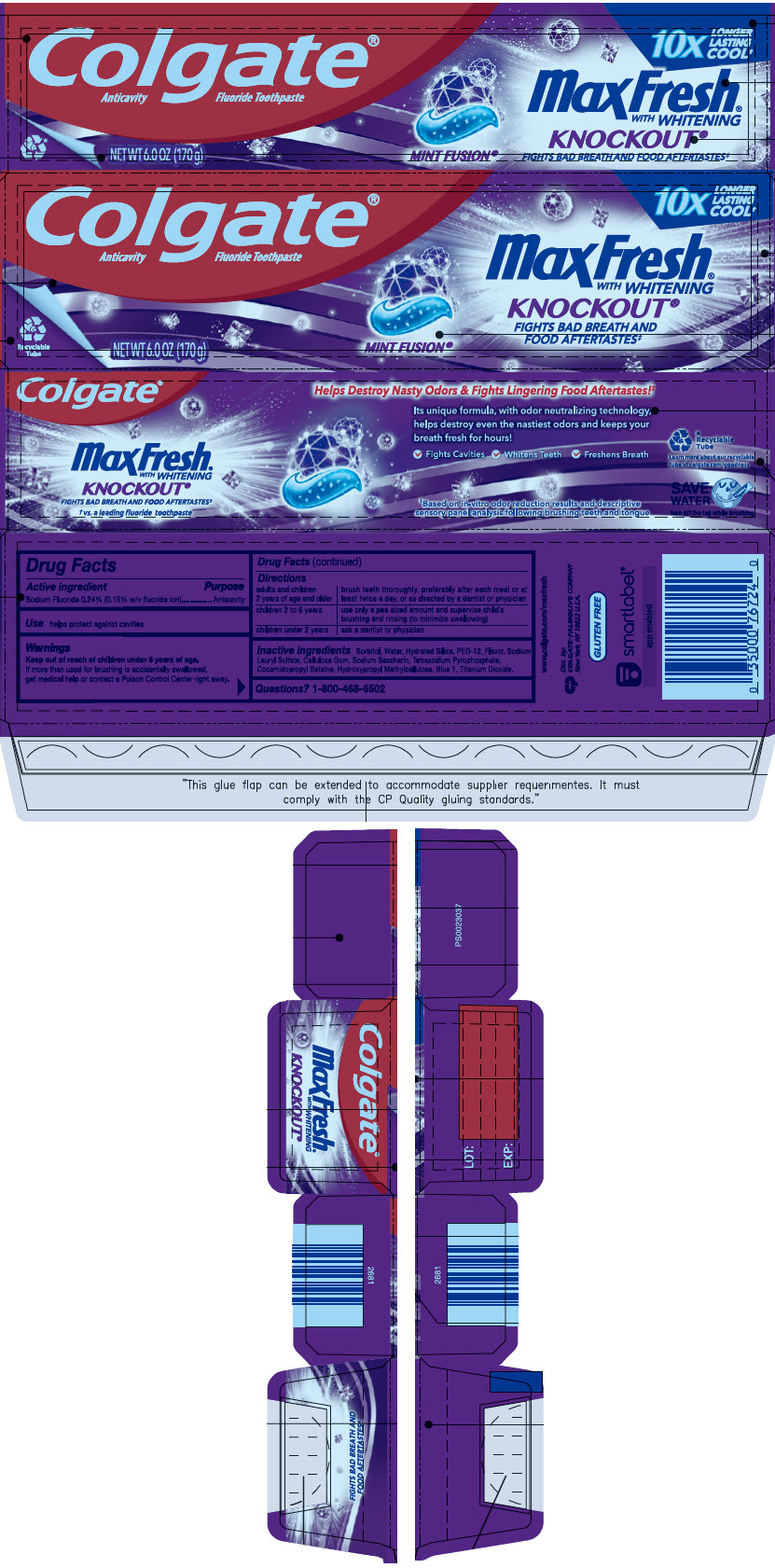 DRUG LABEL: Colgate MaxFresh Knockout
NDC: 35000-127 | Form: PASTE, DENTIFRICE
Manufacturer: COLGATE PALMOLIVE COMPANY
Category: otc | Type: HUMAN OTC DRUG LABEL
Date: 20241113

ACTIVE INGREDIENTS: SODIUM FLUORIDE 1.1 mg/1 g
INACTIVE INGREDIENTS: SORBITOL; WATER; HYDRATED SILICA; POLYETHYLENE GLYCOL 600; SODIUM LAURYL SULFATE; CARBOXYMETHYLCELLULOSE SODIUM, UNSPECIFIED; SACCHARIN SODIUM; SODIUM PYROPHOSPHATE; COCAMIDOPROPYL BETAINE; HYPROMELLOSE, UNSPECIFIED; FD&C BLUE NO. 1; TITANIUM DIOXIDE

Colgate® MaxFresh® Knockout®

Drug Facts

Active ingredient

Sodium Fluoride 0.24% (0.15% w/v fluoride ion)

Purpose

Anticavity

Use

helps protect against cavities

Warnings

Keep out of reach of children under 6 years of age.

If more than used for brushing is accidentally swallowed, get medical help or contact a Poison Control Center right away.

Directions

adults and children 2 years of age and older | brush teeth thoroughly, preferably after each meal or at least twice a day, or as directed by a dentist or physician
children 2 to 6 years | use only a pea sized amount and supervise child's brushing and rinsing (to minimize swallowing)
children under 2 years | ask a dentist or physician

Inactive ingredients

Sorbitol, Water, Hydrated Silica, PEG-12, Flavor, Sodium Lauryl Sulfate, Cellulose Gum, Sodium Saccharin, Tetrasodium Pyrophosphate, Cocamidopropyl Betaine, Hydroxypropyl Methylcellulose, Blue 1, Titanium Dioxide.

Questions?

1-800-468-6502

Dist. by:
COLGATE-PALMOLIVE CO.
New York, NY 10022 U.S.A.

PRINCIPAL DISPLAY PANEL - 170 g Tube Carton

Colgate®
Anticavity Fluoride Toothpaste

10x
LONGER
LASTING
COOL†

MaxFresh®
WITH WHITENING

KNOCKOUT®
FIGHTS BAD BREATH AND
FOOD AFTERTASTES‡

MINT FUSION®

Recyclable
Tube

NET WT 6.0 OZ (170 g)